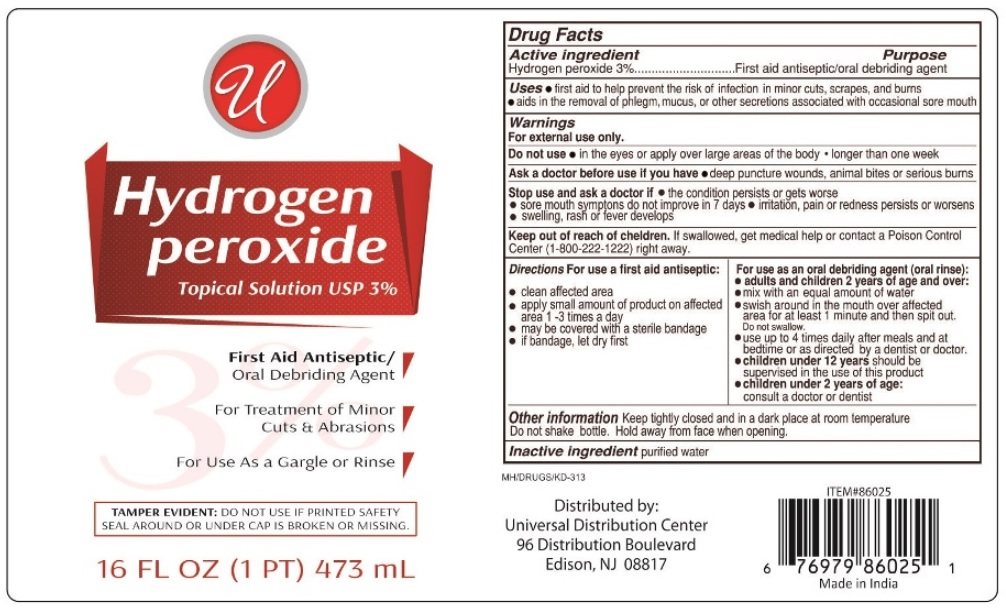 DRUG LABEL: Hydrogen Peroxide
NDC: 52000-025 | Form: LIQUID
Manufacturer: Universal Distribution Center LLC
Category: otc | Type: HUMAN OTC DRUG LABEL
Date: 20201022

ACTIVE INGREDIENTS: HYDROGEN PEROXIDE 3 mL/100 mL
INACTIVE INGREDIENTS: WATER

Hydrogen peroxide Topical Solution USP 3%

Active ingredient

Hydrogen peroxide 3%

Purpose

First aid antiseptic/oral debriding agent

Uses

• first aid to help prevent the risk of infection in minor cuts, scrapes and burns • aids in the removal of phlegm, mucus or other secretions associated with occasional sore mouth

Warnings

For external use only.

Do not use • in the eyes or apply over large areas of the body • longer than one week

Ask a doctor before use if you have • deep puncture wounds, animal bites or serious burns

Stop use and ask a doctor if • the condition persists or gets worse

• sore mouth symptoms do not improve in 7 days • irritation, pain, or redness persists or worsens • swelling, rash or fever develops

Keep out of reach of children. If swallowed, get medical help or contact a Poison Control Center (1-800-222-1222) right away.

DOSAGE AND ADMINISTRATION

Directions For use a first aid antiseptic:

• clean affected area

• apply small amount of product on affected area 1-3 times a day

• may be covered with a sterile bandage

• if bandage, let dry first

For use as an oral debriding agent (oral rinse):

• adults and children 2 years of age and over:

• mix with an equal amount of water

• swish around in the mouth over affected area for at least 1 minute and then spit out. Do not swallow.

• use up to 4 times daily after meals and at bedtime or as directed by a dentist or doctor.

• children under 12 years should be supervised in the use of this product

• children under 2 years of age:

consult a doctor or dentist

Other information

Keep tightly closed and in a dark place at room temperature. Do not shake bottle. Hold away from face when opening.

Inactive ingredient

purified water

Topical Solution USP 3%

First Aid Antiseptic/Oral Debriding Agent

For Treatment of Minor Cuts & Abrasions

For Use As a Gargle or Rinse

TAMPER EVIDENT: DO NOT USE IF PRINTED SAFETY SEAL AROUND OR UNDER CAP IS BROKEN OR MISSING.

Distributed by:

Universal Distribution Center

96 Distribution Boulevard

Edison, NJ 08817

Made in India